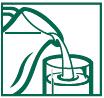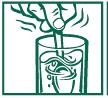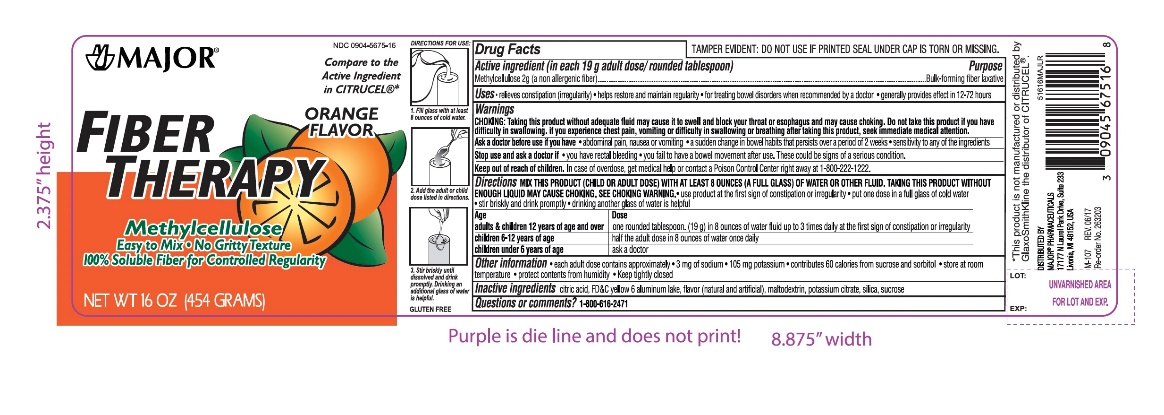 DRUG LABEL: FIBER THERAPY
NDC: 0904-5675 | Form: POWDER, FOR SOLUTION
Manufacturer: Major Pharmaceuticals
Category: otc | Type: HUMAN OTC DRUG LABEL
Date: 20250919

ACTIVE INGREDIENTS: METHYLCELLULOSE (4000 MPA.S) 2 g/19 g
INACTIVE INGREDIENTS: CITRIC ACID MONOHYDRATE; FD&C YELLOW NO. 6; POTASSIUM CITRATE; RIBOFLAVIN; SUCROSE; SILICON DIOXIDE; SORBITOL; TALC

Drug Facts

Active ingredient

(in each 19g adult dose/ rounded tablespoon)

Methylcellulose 2g (a non-allergenic fiber)

Purpose

Bulk-forming fiber laxative

Uses

- relieves constipation (irregularity)
- helps to restore and maintain regularity
- for treating bowel disorders when recommended by a doctor
- generally provide effect in 12-72 hours

Warnings

CHOKING: taking this product without adequate fluid may cause it to swell and block your throat or esophagus and may cause choking. Do not take this product if you have difficulty in swallowing. If you experience chest pain, vomiting, or difficulty in swallowing or breathing after taking this product, seek immediate medical attention.

Ask a doctor before use if you have

- abdominal pain, nausea or vomiting
- a sudden change in bowel habits that persists over a period of 2 weeks
- sensitivity to any of the ingredients

Stop use and ask a doctor if

- you have rectal bleeding
- you fail to have a bowl movement after use.
- These could be signs of a serious condition.

Keep out of reach of children.

In case of overdose, get medical help or contact a Poison Control Center right away at 1-800-222-1222.

When using this product

- do not exceed recommended maximum daily dose unless directed by a doctor
- do not use laxative products for a period longer than one week unless directed by a doctor

Directions

- MIX THIS PRODUCT (CHILD OR ADULT DOSE) WITH AT LEAST 8 OUNCES (A FULL GLASS) OF WATER OR OTHER FLUID. TAKING THIS PRODUCT WITHOUT ENOUGH LIQUID MAY CAUSE CHOKING. SEE CHOKING WARNING
- use product at the first sign of constipation or irregularity
- put one dose in a full glass of cold water
- stir briskly and drink promptly
- drinking another glass of water is helpful

Age | Dose
adults & children above 12 years of age and over | One rounded tablespoon. (19 g) in 8 ounces of water fluid up to 3 times daily at the first sign of constipation or irregularity
children 6 - 12 years of age; Children under 6 years of age | half the adult dose in 8 ounces of water once daily.; ask a doctor

Other information

- Each adult dose contains approximately
- 3mg of sodium
- 105mg potassium
- contributes 60 calories from sucrose and sorbitol
- store at room temperature
- protect contents from humidity
- keep tightly closed

Tamper Evident: Do not use if printed seal under cap is torn or missing

Inactive ingredients

citric acid, FD&C yellow 6 aluminum lake, maltodextrin, flavor (natural and artificial), potassium citrate, , silica, sucrose,

Questions or comments?

call toll-free 1-800-616-2471

*This product is not manufactured or distributed by GlaxoSmithKline the distributor of CITRUCEL®

Distributed by:

MAJOR®PHARMACEUTICALS

17177 N Laurel Park Drive, Suite 233

Livonia, MI 48152, USA

DIRECTIONS FOR USE

1. Fill glass with at least 8 ounces of cold water.

2. Add the adult or child dose listed in the directions. 3. Stir briskly until dissolved and drink promptly. Drinking an additional glass of water is helpful.

BOXED WARNING

TAMPER EVIDENT PACKAGE

Do not use if printed seal under cap is torn or missing.

Principal Display Panel

NDC 0904-5675-16

FIBER THERAPY

Methylcellulose

Easy to Mix

No Gritty Texture

100% Soluble Fiber for Controlled Regularity

ORANGE FLAVOR

NET WT 16 OZ (454 GRAMS)